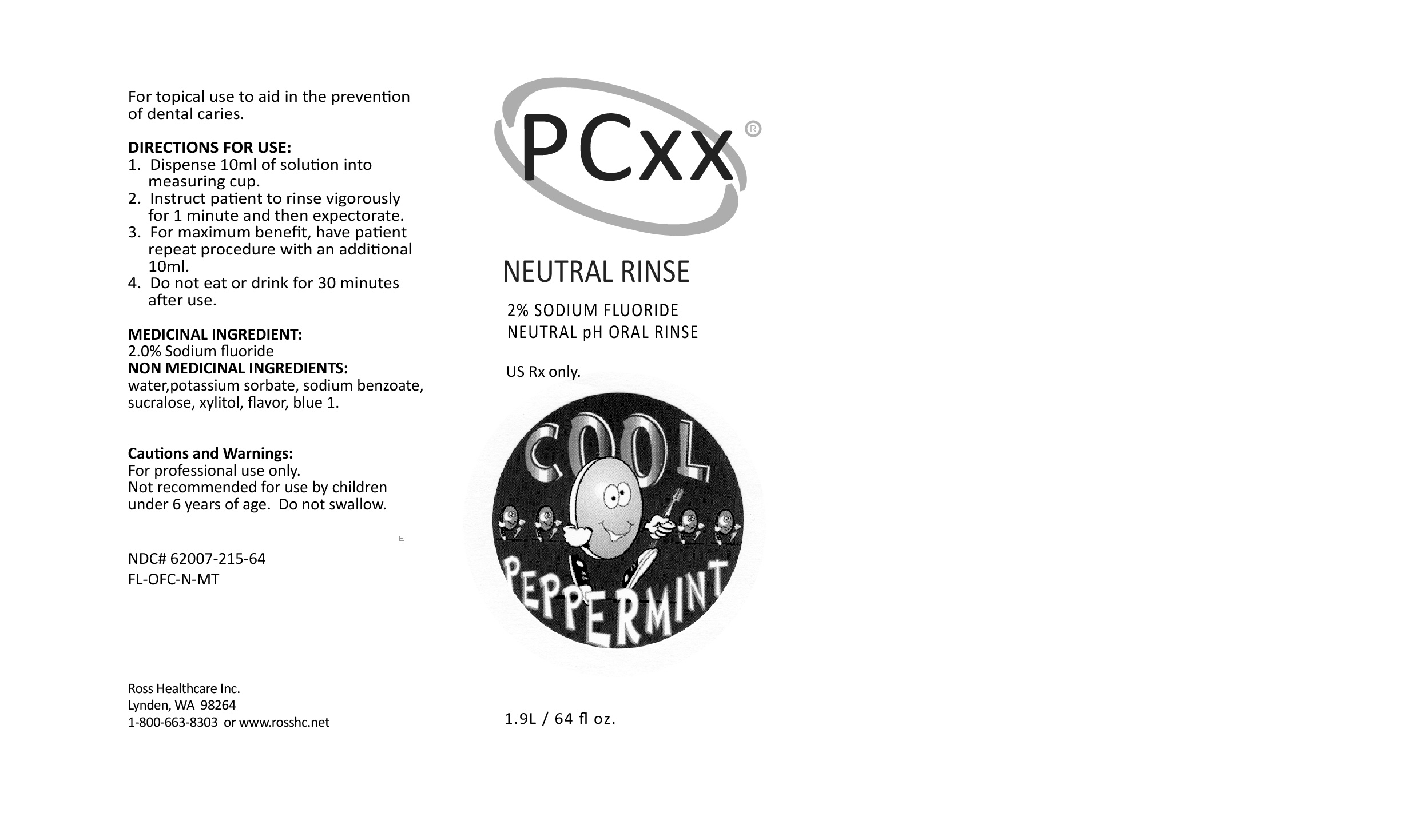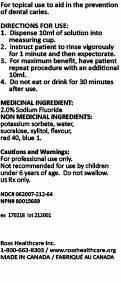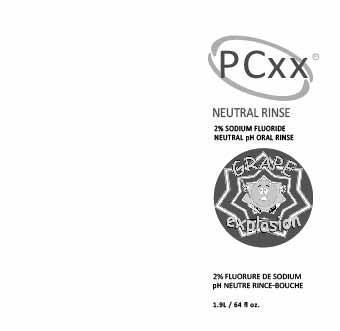 DRUG LABEL: PCXX NEUTRAL RNS PEPPERMINT
NDC: 62007-215 | Form: RINSE
Manufacturer: Ross Healthcare Inc.
Category: prescription | Type: HUMAN PRESCRIPTION DRUG LABEL
Date: 20251106

ACTIVE INGREDIENTS: SODIUM FLUORIDE 2 mg/1 mL
INACTIVE INGREDIENTS: SODIUM BENZOATE 0.1 mg/1 mL; XYLITOL 1 mg/1 mL

PCXX NEUTRAL RNS PEPPERMINT